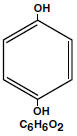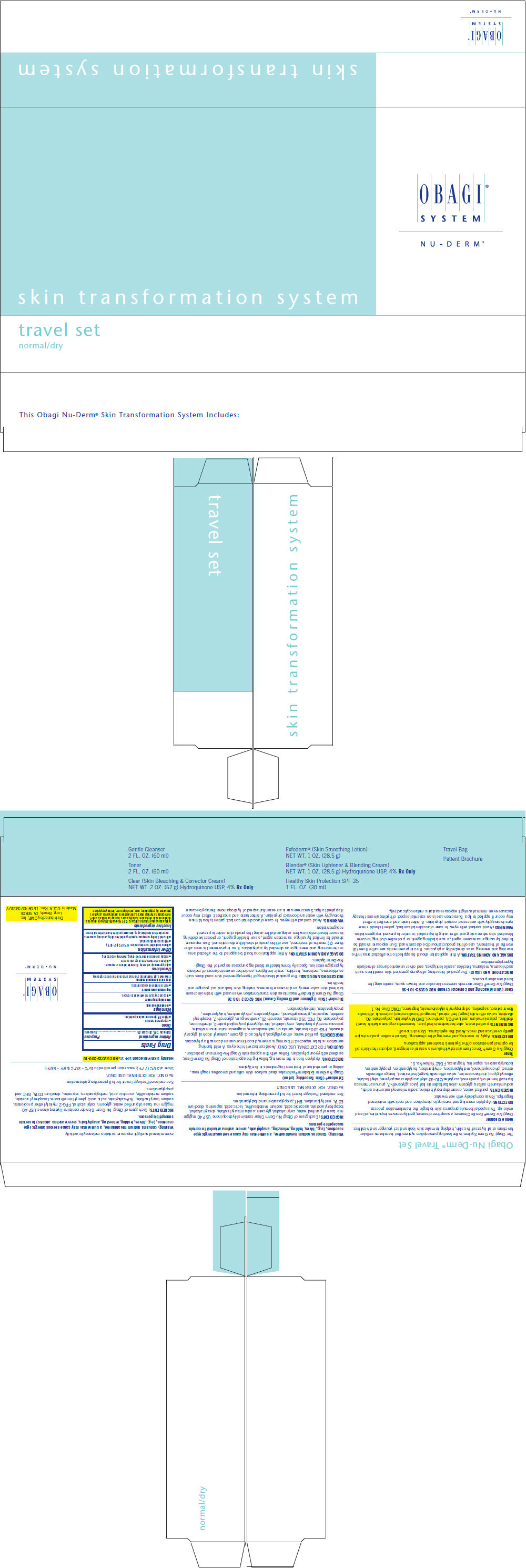 DRUG LABEL: nu-derm travel set normal/dry 
NDC: 62032-500 | Form: KIT | Route: TOPICAL
Manufacturer: Obagi Cosmeceuticals LLC
Category: prescription | Type: HUMAN PRESCRIPTION DRUG LABEL
Date: 20191204

ACTIVE INGREDIENTS: HYDROQUINONE 40 mg/1 g; HYDROQUINONE 40 mg/1 g; OCTINOXATE 75 mg/1 mL; ZINC OXIDE 90 mg/1 mL
INACTIVE INGREDIENTS: EDETATE DISODIUM; PPG-2 MYRISTYL ETHER PROPIONATE; TROLAMINE SALICYLATE; SODIUM LAURYL SULFATE; CETYL ALCOHOL; GLYCERIN; LACTIC ACID, UNSPECIFIED FORM; .ALPHA.-TOCOPHEROL ACETATE; ASCORBIC ACID; SODIUM METABISULFITE; WATER; METHYLPARABEN; PROPYLPARABEN; BUTYLATED HYDROXYTOLUENE; PHENYL TRIMETHICONE; EDETATE DISODIUM; BUTYLPARABEN; STEARYL ALCOHOL; SODIUM LAURYL SULFATE; CETYL ALCOHOL; GLYCERIN; LACTIC ACID, UNSPECIFIED FORM; .ALPHA.-TOCOPHEROL ACETATE; ASCORBIC ACID; SODIUM METABISULFITE; WATER; METHYLPARABEN; PROPYLPARABEN; BUTYLATED HYDROXYTOLUENE; ISOPROPYL PALMITATE; WATER; ETHYLHEXYL STEARATE; CETOSTEARYL ALCOHOL; POLYSORBATE 60; C13-14 ISOPARAFFIN; METHYLPARABEN; LAURETH-7; PROPYLPARABEN; EDETATE DISODIUM; BUTYLPARABEN; DIETHANOLAMINE CETYL PHOSPHATE; PHENOXYETHANOL; ETHYLPARABEN; ISOBUTYLPARABEN; SODIUM HYDROXIDE; TRIETHOXYCAPRYLYLSILANE; CITRIC ACID MONOHYDRATE

Obagi Nu-Derm Clear
(Hydroquinone USP, 4%)
Skin Bleaching Cream
Obagi Nu-Derm Blender®
(Hydroquinone USP, 4%)
Skin Bleaching Cream
Obagi Nu-Derm Sunfader®
(Hydroquinone USP, 4%,
Octinoxate USP, 7.5%
and Oxybenzone USP, 5.5%)
Skin Bleaching Cream with Sunscreens

Rx Only

FOR EXTERNAL USE ONLY

DESCRIPTION

Hydroquinone is 1,4-benzenediol. Hydroquinone occurs as fine, white needles. The drug is freely soluble in water and in alcohol. Chemically, hydroquinone is designated as p-dihydroxybenzene; the empirical formula is C6 H6 O2; molecular weight is 110.0.

Each gram of Obagi Nu-Derm Blender contains Hydroquinone USP 40 mg/gm in a base of purified water, glycerin, cetyl alcohol, PPG-2 myristyl ether propionate, sodium lauryl sulfate, TEA-salicylate, lactic acid, phenyl trimethicone, tocopheryl acetate, sodium metabisulfite, ascorbic acid, methylparaben, saponins, disodium EDTA, BHT, and propylparaben.

Each gram of Obagi Nu-Derm Clear contains Hydroquinone USP 40 mg/gm in a base of purified water, cetyl alcohol, glycerin, sodium lauryl sulfate, stearyl alcohol, tocopheryl acetate, ascorbic acid, sodium metabisulfite, lactic acid, saponins, disodium EDTA, methylparaben, BHT, propylparaben, and butylparaben.

Each gram of Obagi Nu-Derm Sunfader contains Hydroquinone USP 40 mg/gm, Octinoxate USP, 7.5%, and Oxybenzone USP, 5.5%, in a base of purified water, cetyl alcohol, glycerin, sodium lauryl sulfate, stearyl alcohol, tocopheryl acetate, ascorbic acid, sodium metabisulfite, disodium EDTA, methylparaben, saponins, propylparaben, BHT, and butylparaben.

CLINICAL PHARMACOLOGY

Topical application of hydroquinone produces a reversible depigmentation of the skin by inhibition of the enzymatic oxidation of tyrosine to 3, 4-dihydroxyphenylalanine (dopa) and suppression of other melanocyte metabolic processes.

Exposure to sunlight or ultraviolet light will cause repigmentation of the bleached areas, which may be prevented by the use of sunblocking agents or sunscreen agents contained in Obagi Nu-Derm Sunfader.

INDICATIONS AND USAGE

The gradual bleaching of hyperpigmented skin conditions such as chloasma, melasma, freckles, senile lentigines, and other unwanted areas of melanin hyperpigmentation. Obagi Nu-Derm Sunfader is intended for daytime use as it contains sunscreen agents.

CONTRAINDICATIONS

Prior history of sensitivity or allergic reaction to this product or any of its ingredients. The safety of topical hydroquinone use during pregnancy or in children (12 years and under) has not been established.

WARNINGS

Caution

Hydroquinone is a skin bleaching agent which may produce unwanted cosmetic effects if not used as directed. The physician should be familiar with the contents of this insert before prescribing or dispensing this medication.

Test for skin sensitivity before using by applying a small amount to an unbroken patch of skin and check in 24 hours. Minor redness is not a contraindication, but where there is itching or vesicle formation or excessive inflammatory response, further treatment is not advised. Close patient supervision is recommended.

Avoid contact with eyes. In case of accidental contact, patient should rinse eyes thoroughly with water and contact physician. A bitter taste and anesthetic effect may occur if applied to lips.

Sunscreen use is an essential aspect of hydroquinone therapy because even minimal sunlight exposure sustains melanocytic activity. Obagi Sunfader is formulated for use as a skin bleaching agent and should not be used for the prevention of sunburn.

Warning

Contains sodium metabisulfite, a sulfite that may cause serious allergic type reactions (e.g., hives, itching, wheezing, anaphylaxis, severe asthma attacks) in certain susceptible persons.

PRECAUTIONS

(SEE WARNINGS)

General

Treatment should be limited to relatively small areas of the body at one time since some patients experience a transient skin reddening and a mild burning sensation which does not preclude treatment.

Pregnancy Category C

Animal reproduction studies have not been conducted with topical hydroquinone. It is also not known whether hydroquinone can cause fetal harm when used topically on a pregnant woman or affect reproductive capacity. It is not known to what degree, if any, topical hydroquinone is absorbed systemically. Topical hydroquinone should be used on pregnant women only when clearly indicated.

Nursing mothers

It is not known whether topical hydroquinone is absorbed or excreted in human milk. Caution is advised when topical hydroquinone is used by a nursing mother.

Pediatric usage

Safety and effectiveness in children below the age of 12 years have not been established.

ADVERSE REACTIONS

No systemic adverse reactions have been reported. Occasional hypersensitivity (localized contact dermatitis) may occur, in which case the medication should be discontinued and the physician notified immediately.

DOSAGE AND ADMINISTRATION

A thin application should be applied to the affected area twice daily or as directed by a physician. If no improvement is seen after three (3) months of treatment, use of this product should be discontinued. Sun exposure should be limited by using a sunscreen agent, a sun blocking agent, or protective clothing to cover bleached skin when using and after using this product in order to prevent repigmentation.

HOW SUPPLIED

Obagi Nu-Derm Blender is available as follows:

2 oz. (57 gm) bottle | NDC 62032-100-36
1 oz. (28.5 gm) bottle | NDC 62032-100-10

Obagi Nu-Derm Clear is available as follows:

2 oz. (57 gm) bottle | NDC 62032-101-36
1 oz. (28.5 gm) bottle | NDC 62032-101-10

Obagi Nu-Derm Sunfader is available as:

2 oz. (57 gm) bottle | NDC 62032-116-36

STORAGE AND HANDLING

Store at 25°C (77°F); excursion permitted to 15°C-30°C (59°F-86°F).

OMP, Inc.
Long Beach, CA 90802
USA
1-800-636-7546

Rev. 8/03

PRINCIPAL DISPLAY PANEL - Kit Carton

OBAGI®
SYSTEM

NU - DERM®

skin transformation system

travel set
normal/dry